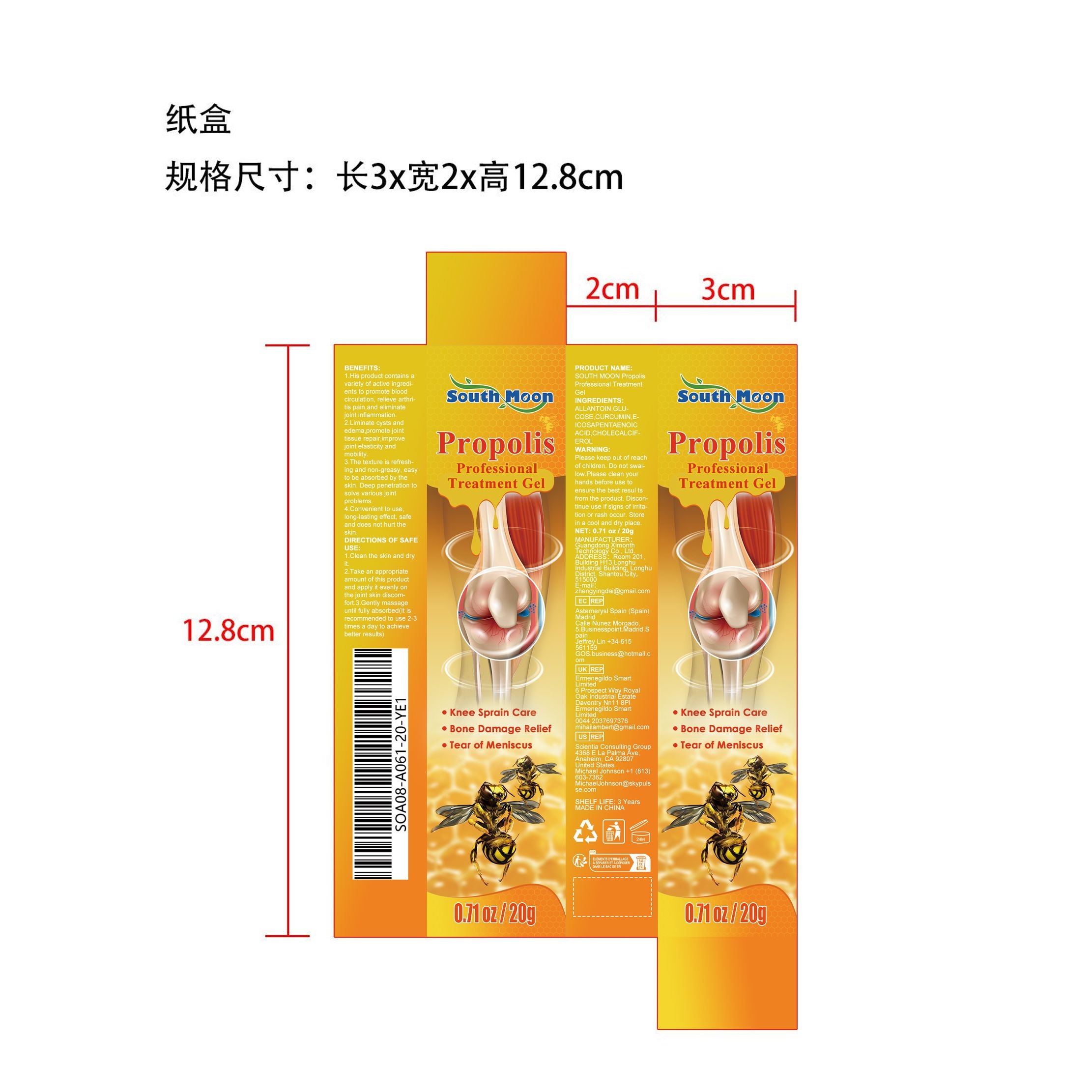 DRUG LABEL: SOUTH MOON Propolis Professional Treatment Gel
NDC: 84660-034 | Form: GEL
Manufacturer: Guangdong Ximonth Technology Co., Ltd.
Category: otc | Type: HUMAN OTC DRUG LABEL
Date: 20240926

ACTIVE INGREDIENTS: ANHYDROUS DEXTROSE 5 g/20 g; CURCUMIN 4 g/20 g; ICOSAPENT 3 g/20 g; CHOLECALCIFEROL 2 g/20 g
INACTIVE INGREDIENTS: ALLANTOIN 6 g/20 g

Active Ingredient(s)

GLUCOSE、CURCUMIN、EICOSAPENTAENOIC ACID、CHOLECALCIFEROL

Purpose

1.His product contains a variety of active ingredients to promote blood circulation, relieve arthritis pain,and eliminate joint inflammation.
2.Liminate cysts and edema,promote joint tissue repair,improve joint elasticity and mobility.
3.The texture is refreshing and non-greasy, easy to be absorbed by the skin. Deep penetration to solve various joint problems.
4.Convenient to use, long-lasting effect, safe and does not hurt the skin.

Use

1.Clean the skin and dry it.
2.Take an appropriate amount of this product and apply it evenly on the joint skin discomfort.
3.Gently massage until fully absorbed(It is recommended to use 2-3 times a day to achieve better results)

Warnings

Please keep out of reach of children.Do not swallow.Please clean your hands before use to ensure the best results from the product.Discontinue use if signs of irritation or rash occur.Store in a cool and dry place.

Do not use

Discontinue use if signs of irritation or rash occur.

STOP USE

Discontinue use if signs of irritation or rash occur.

KEEP OUT OF REACH OF CHILDREN

Please keep out of reach of children. Do not swallow.

STORAGE AND HANDLING

Avoid freezing and excessive heat above 40C (104F) ）
Store in a cool and dry place.

INACTIVE INGREDIENT

ALLANTOIN